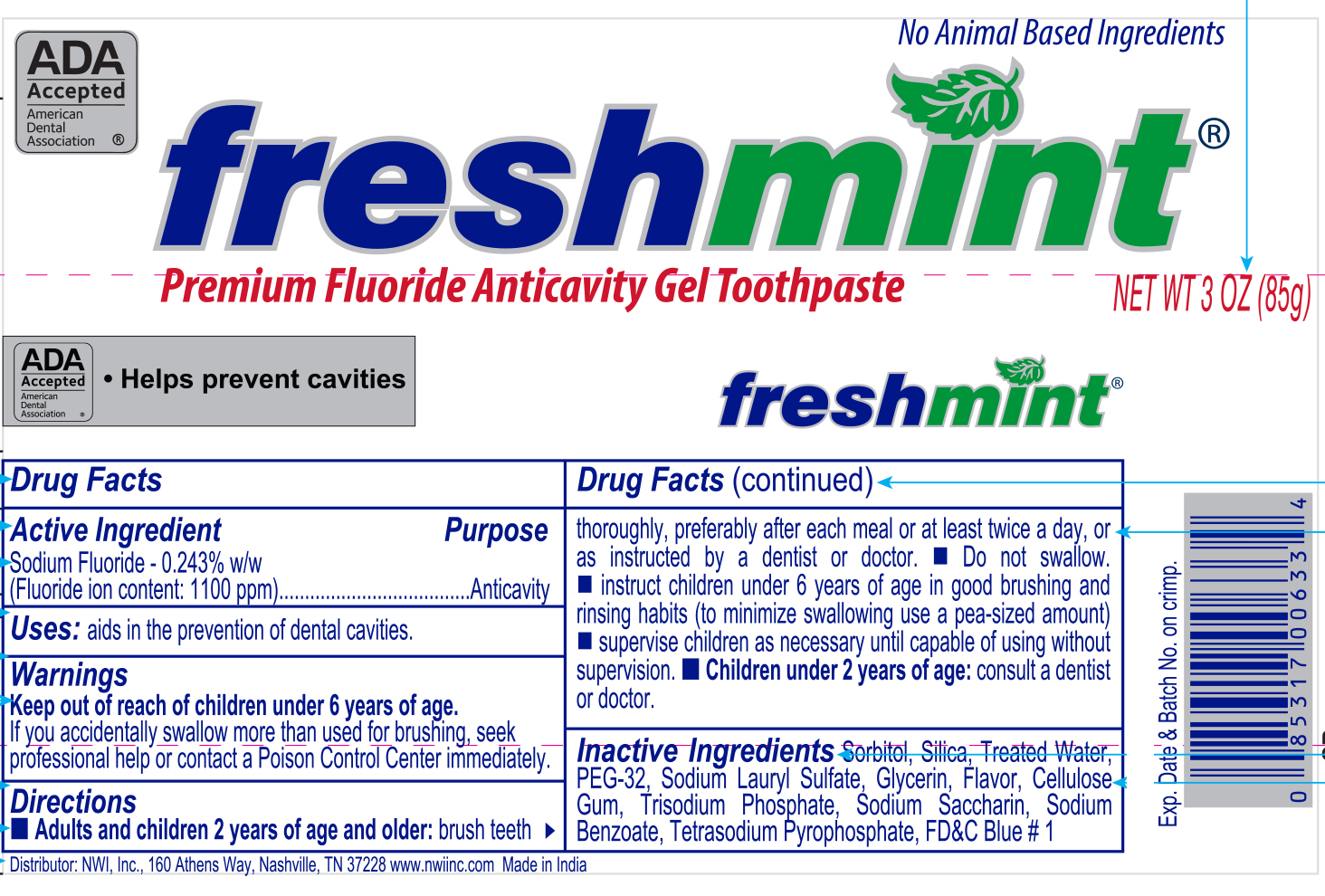 DRUG LABEL: Freshmint Premium Anticavity Gel
NDC: 51824-046 | Form: PASTE, DENTIFRICE
Manufacturer: New World Imports, Inc
Category: otc | Type: HUMAN OTC DRUG LABEL
Date: 20251201

ACTIVE INGREDIENTS: SODIUM FLUORIDE 2.43 mg/1 g
INACTIVE INGREDIENTS: SORBITOL; SILICON DIOXIDE; WATER; POLYETHYLENE GLYCOL 1600; SODIUM LAURYL SULFATE; GLYCERIN; CARBOXYMETHYLCELLULOSE SODIUM, UNSPECIFIED; SODIUM PHOSPHATE, TRIBASIC, DODECAHYDRATE; SODIUM BENZOATE; SODIUM PYROPHOSPHATE; FD&C BLUE NO. 1; SACCHARIN SODIUM

OTC Active Ingredient

Sodium Fluoride - 0.243% (Fluoride ion content: 1100 ppm)

OTC Purpose

Anticavity

Keep out of reach of Children under 6 years of age

If you accidentally swallow more than used for brushing, seek professional help or contact a Poison Control Center immediately.

Uses

Aids in the prevention of dental cavities

Warnings

Keep out of reach of children under 6 years of age.if you accidentally swallow more than used for brushing, seek professional help or contact a Poison Control Center immediately.

Directions

Adults and children 2 years & older:

- Brush teeth thoroughly after meals or at least twice a day or use as instructed by a dentist.
- Do not swallow.
- Instruct children under 6 years of age in good brushing and rinsing habits (to minimize swallowing use a pea-sized amount)
- Supervise children's brushing until capable of using without supervision

Children under 2 years:

- consult a dentist or doctor

Inactive Ingredients

Sorbitol, Silica, Treated Water, PEG-32, Sodium Lauryl Sulfate, Glycerin, Flavor, Cellulose Gum, Trisodium Phosphate, Sodium Saccarin, Sodium Benzoate, Tetrasodium Pyrophosphate, FD&C Blue # 1